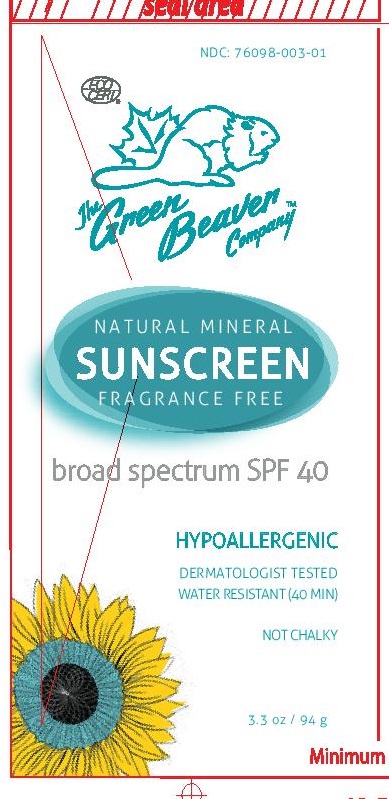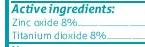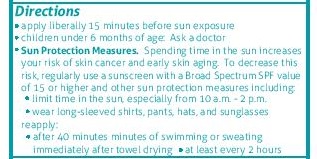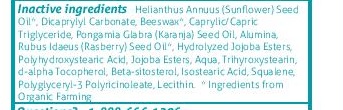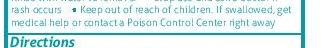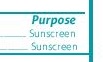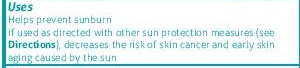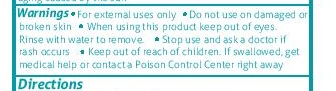 DRUG LABEL: The Green Beaver Company SPF 40 Adult Sunscreen
NDC: 76098-003 | Form: LOTION
Manufacturer: The Green Beaver Company
Category: otc | Type: HUMAN OTC DRUG LABEL
Date: 20210111

ACTIVE INGREDIENTS: ZINC OXIDE 8 g/100 g; TITANIUM DIOXIDE 8 g/100 g
INACTIVE INGREDIENTS: CEROTIC ACID; HYDROLYZED JOJOBA ESTERS (ACID FORM); ALUMINUM OXIDE; POLYGLYCERYL-3 RICINOLEATE; TRIHYDROXYSTEARIN; .ALPHA.-TOCOPHEROL ACETATE, D-; SODIUM BETA-SITOSTERYL SULFATE; SQUALENE; LECITHIN, SUNFLOWER; KARUM SEED OIL; HELIANTHUS ANNUUS SEED WAX; DICAPRYLYL CARBONATE; CAPRYLIC/CAPRIC/LAURIC TRIGLYCERIDE; RUBUS IDAEUS FRUIT VOLATILE OIL; POLYHYDROXYSTEARIC ACID (2300 MW); WATER; ISOSTEARIC ACID

The Green Beaver Adults Sunscreen SPF 40